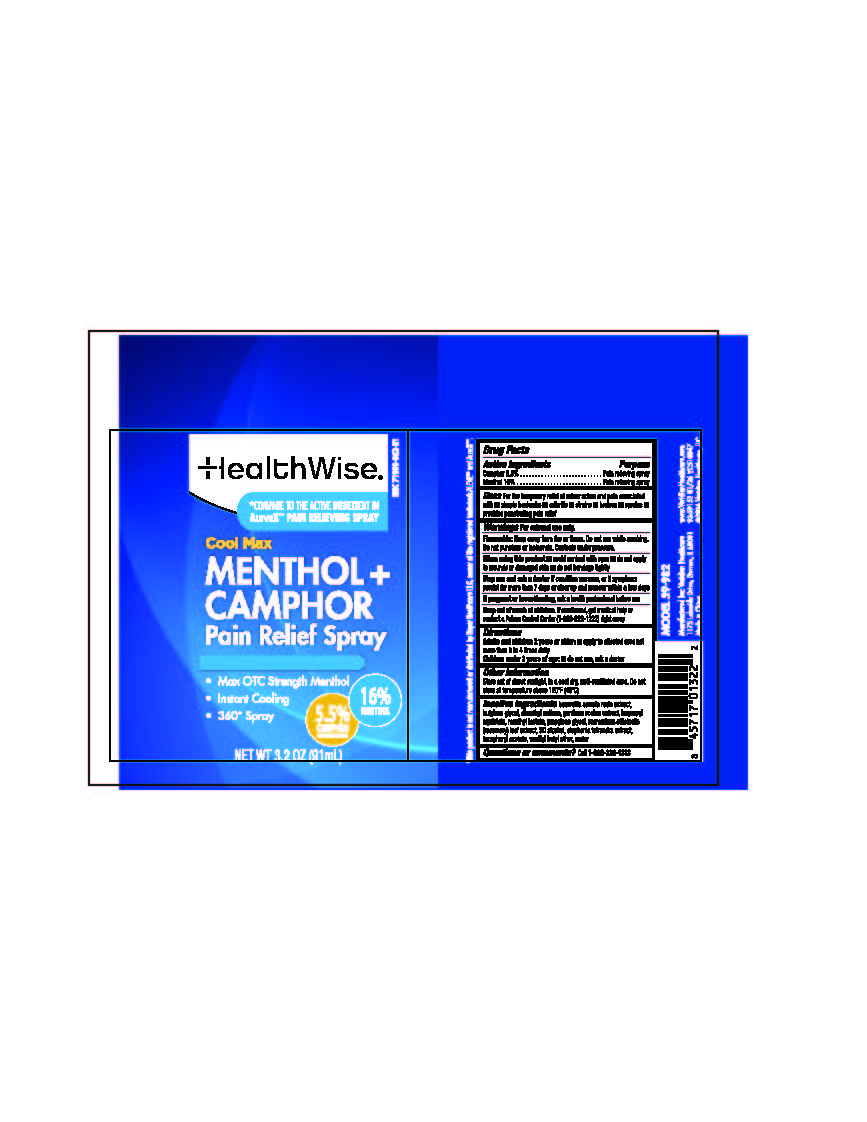 DRUG LABEL: Menthol plus Camphor Pain Relief
NDC: 71101-982 | Form: SPRAY
Manufacturer: Veridian Healthcare
Category: otc | Type: HUMAN OTC DRUG LABEL
Date: 20260204

ACTIVE INGREDIENTS: CAMPHOR (NATURAL) 5.5 g/100 mL; MENTHOL 16 g/100 mL
INACTIVE INGREDIENTS: BUTYLENE GLYCOL; BOSWELLIA SERRATA GUM; VANILLYL BUTYL ETHER; .ALPHA.-TOCOPHEROL ACETATE; STEPHANIA TETRANDRA ROOT; GENTIANA SCABRA WHOLE; ISOPROPYL MYRISTATE; METHYL LACTATE; ALCOHOL; PROPYLENE GLYCOL; DIMETHYL SULFONE; WATER; ROSMARINUS OFFICINALIS (ROSEMARY) LEAF POWDER

HealthWise Menthol + Camphor Pain Relief Spray

Drug Facts

Active Ingredients

Camphor 5.5%
Menthol 16%

Purpose

Pain relieving spray

Uses

for temporary relief of minor pain and associated with:

- simple backache
- arthritis
- strains
- bruises
- sprains
- provides penetrating pain relief

Warnings

For external use only

Flammable Do not use while smoking or near heat of flame. Do not use while smoking. Do not punture or incinerate. Contents under pressure.

When using this product

- avoid contact with eyes
- do not apply to wounds or damage skin
- do not bandage tightly

Stop use and ask a doctor if

- condition worsens
- or if symptoms persist for more than 7 days or clear up and reoccur within a few days.

If pregnant or breastfeeding

ask a health professional before use

Keep out of reach of children.

If swallowed, get medical help or contact a Poison Control Center (1-800-222-1222) right away.

Directions

- adults and children 2 years and older:apply to affected area not more than 3 to 4 times daily.
- children under 2 years of age:do not use, ask a doctor

Other information

- Store out of direct sunlight, in a cool dry well-ventilated area. Do not store at temperature above 120F (49C)

Inactive ingredients

boswellia serrata resin extract, butylene glycol, dimethyl sulfone, gentiana scabra extract, isopropyl myristate, methyl lactate, propylene glycol, rosmarinus officinalis (rosemary) leaf extract, SD alcohol, srephania tetrandra extract, tocopheryl acetate, vanillyl butyl ether, water